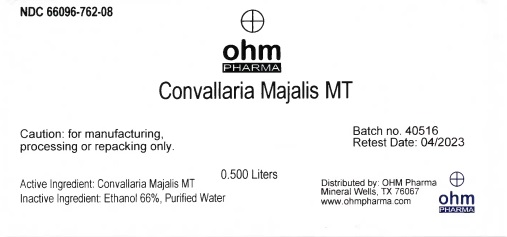 DRUG LABEL: Convallaria Majalis MT
NDC: 66096-762 | Form: LIQUID
Manufacturer: OHM PHARMA INC.
Category: homeopathic | Type: HUMAN OTC DRUG LABEL
Date: 20211229

ACTIVE INGREDIENTS: CONVALLARIA MAJALIS 1 [hp_X]/0.5 L
INACTIVE INGREDIENTS: WATER; ALCOHOL

Convallaria Majalis MT

Active Ingredient: Convallaria Majalis MT

WARNINGS

Caution: for manufacturing,

processing or repacking only.

Inactive Ingredient:

Ethanol 66%, Purified Water.

QUESTIONS

Distributed by: OHM PHARMA

Mineral Wells, TX 76067

www.ohmpharma.com

PACKAGE LABEL

NDC: 66096-762-08

ohm

PHARMA

Convallaria Majalis MT

0.500 Liters

Caution: for manufacturing,

processing or repacking only.

Batch no. 40516

Retest Date: 04/2023

Active Ingredient: Convallaria Majalis MT

Inactive Ingredient: Ethanol 66%, Purified Water

Distributed by OHM Pharma

Mineral Wells, TX 76067

www.ohmpharma.com